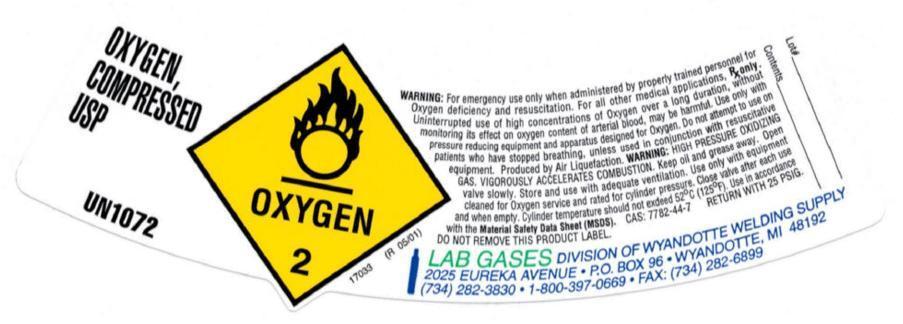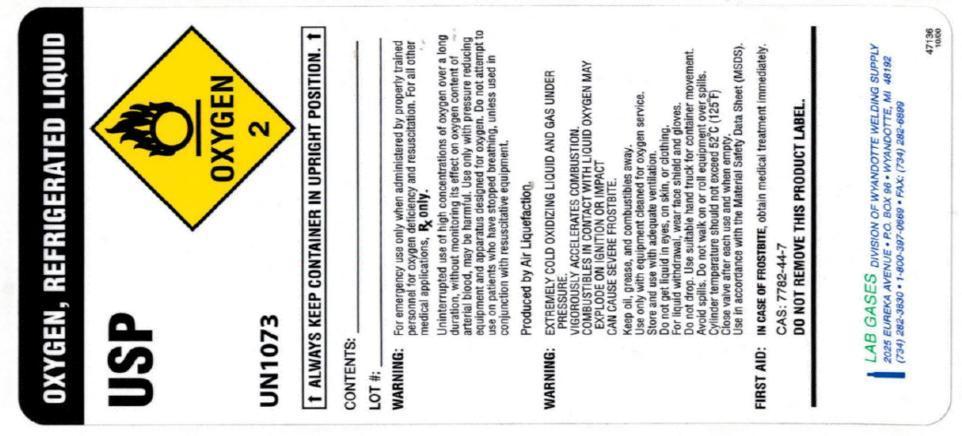 DRUG LABEL: Oxygen
NDC: 63045-001 | Form: GAS
Manufacturer: Wyandotte Welding Supply Inc.
Category: prescription | Type: HUMAN PRESCRIPTION DRUG LABEL
Date: 20140502

ACTIVE INGREDIENTS: Oxygen 990 mL/1 L

Oxygen

PACKAGE LABEL

OXYGEN, COMPRESSED USP
UN 1072
OXYGEN2
WARNING: For emergency use only when administered by properly trained personnel for Oxygen deficiency and resuscitation. For all other medical applications, Rx only. Uninterrupted use of high concentrations of Oxygen over a long duration, without monitoring its effect on oxygen content of arterial blood, may be harmful. Use only with pressure reducing equipment and apparatus designed for Oxygen. Do not attempt to use on patients who have stopped breathing, unless used in conjunction with resuscitative equipment. Produced by Air Liquefaction. WARNING: HIGH PRESSURE OXIDIZING GAS. VIGOROUSLY ACCELERATES COMBUSTION. Keep oil and grease away. Open valve slowly. Store and use with adequate ventilation. Use only with equipment cleaned for Oxygen service and rated for cylinder pressure. Close valve after each use and when empty. Cylinder temperature should not exceed 52 degrees C (125 degrees F). Use in accordance with the Material Safety Data Sheet (MSDS). CAS: 7782-44-7. RETURN WITH 25 PSIG. DO NOT REMOVE THIS PRODUCT LABEL.
LAB GASES DIVISION OF WYANDOTTE WELDING SUPPLY
2025 EUREKA AVENUE PO BOX 96
WYANDOTTE, MI 48192
(734) 282-3830 1-800-397-0669
FAX: (734) 282-6899
Lot #
Contents:

PACKAGE LABEL

OXYGEN, REFRIGERATED LIQUID USP UN1073 OXYGEN 2
ALWAYS KEEP CONTAINER IN UPRIGHT POSITION.
CONTENTS:
LOT #:
WARNING: For emergency use only when administered by properly trained personnel for oxygen deficiency and resuscitation. For all other medical applications, Rx Only.
Uninterrupted use of high concentrations of oxygen over a long duration, without monitoring its effect on oxygen content of arterial blood, may be harmful. Use only with pressure reducing equipment and apparatus designed for oxygen. Do not attempt to use on patients who have stopped breathing, unless used in conjunction with resuscitative equipment.
Produce by Air Liquefaction.
WARNING: EXTREMELY COLD, OXIDIZING LIQUID AND GAS UNDER PRESSURE. VIGOROUSLY ACCELERATES COMBUSTION. COMBUSTIBLES IN CONTACT WITH LIQUID OXYGEN MAY EXPLODE ON IGNITION OR IMPACT. CAN CAUSE SEVERE FROSTBITE.
Keep oil, grease, and combustibles away. Use only with equipment cleaned for oxygen service. Store and use with adequate ventilation. Do not get liquid in eyes, on skin, or clothing. For liquid withdrawal, wear face shield and gloves. Do not drop. Use suitable hand truck for container movement. Avoid spills. Do not walk on or roll equipment over spills. Cylinder temperature should not exceed 52 degrees C (125 degrees F). Close valve after each use and when empty. Use in accordance with the Material Safety Data Sheet (MSDS).
FIRST AID: IN CASE OF FROSTBITE, obtain medical treatment immediately.
CAS: 7782-44-7
DO NOT REMOVE THIS PRODUCT LABEL.
LAB GASES DIVISION OF WYANDOTTE WELDING SUPPLY
2025 EUREKA AVENUE PO BOX 96
WYANDOTTE, MN 48192
(734) 282-3830 1-800-397-0669
FAX: (734) 282-6899